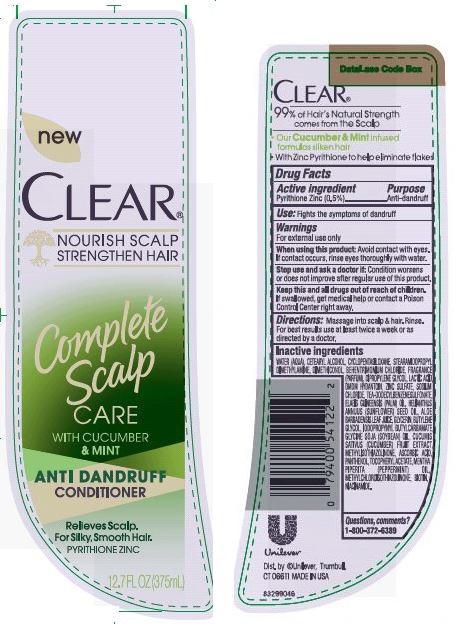 DRUG LABEL: Clear
NDC: 64942-1435 | Form: SUSPENSION
Manufacturer: Conopco Inc. d/b/a Unilever
Category: otc | Type: HUMAN OTC DRUG LABEL
Date: 20150922

ACTIVE INGREDIENTS: Pyrithione Zinc 0.5 g/100 mL
INACTIVE INGREDIENTS: WATER; CETOSTEARYL ALCOHOL; CYCLOMETHICONE 5; SODIUM CHLORIDE; STEARAMIDOPROPYL DIMETHYLAMINE; BEHENTRIMONIUM CHLORIDE; DMDM HYDANTOIN; TRIETHANOLAMINE DODECYLBENZENESULFONATE; DIPROPYLENE GLYCOL; LACTIC ACID; ZINC SULFATE; METHYLCHLOROISOTHIAZOLINONE; METHYLISOTHIAZOLINONE; PEPPERMINT OIL; SUNFLOWER OIL; PALM OIL; GLYCERIN; BUTYLENE GLYCOL; .ALPHA.-TOCOPHEROL ACETATE, D-; DIMETHICONOL (41 MPA.S); ASCORBIC ACID; PANTHENOL; BIOTIN; NIACINAMIDE

Clear Complete Scalp Care AntiDandruff Conditioner

Active Ingredient

Pyrithione Zinc (0.5%)

PURPOSE

PurposeAnti-dandruff

INDICATIONS AND USAGE

Use: Fights the symptoms of dandruff

Warnings
For external use only

When using this product: Avoid contact with eyes. If contact occurs, rinse eyes thoroughly with water.

Stop use and ask a doctor if: Condition worsens or does not improve after regular use of this product.

KEEP OUT OF REACH OF CHILDREN

Keep this and all drugs out of reach of children. If swallowed, get medical help or contact a Poison Control Center right away.

DOSAGE AND ADMINISTRATION

Directions: Massage into scalp & hair. Rinse. For best results use at least twice a week or as directed by a doctor.

Inactive Ingredients

Water (Aqua), Cetearyl Alcohol, Cyclopentasiloxane, Stearamidopropyl Dimethylamine, Dimethiconol, Behentrimonium Chloride, Fragrance (Parfum), Dipropylene Glycol, Lactic Acid, DMDM Hydantoin, Zinc Sulfate, Sodium Chloride, TEA-Dodecylbenzenesulfonate, Elaeis Guineensis (Palm) Oil, Helianthus Annuus (Sunflower) Seed Oil, Aloe Barbadensis Leaf Juice, Glycerin, Butylene Glycol, Iodopropynyl Butylcarbamate, Glycine Soja (Soybean) Oil, Cucumis Sativus (Cucumber) Fruit Extract, Methylisothiazolinone, Ascorbic Acid, Panthenol, Tocopheryl Acetate, Mentha Piperita (Peppermint) Oil, Methylchloroisothiazolinone, Biotin, Niacinamide.

Questions, comments?

1-800-372-6389